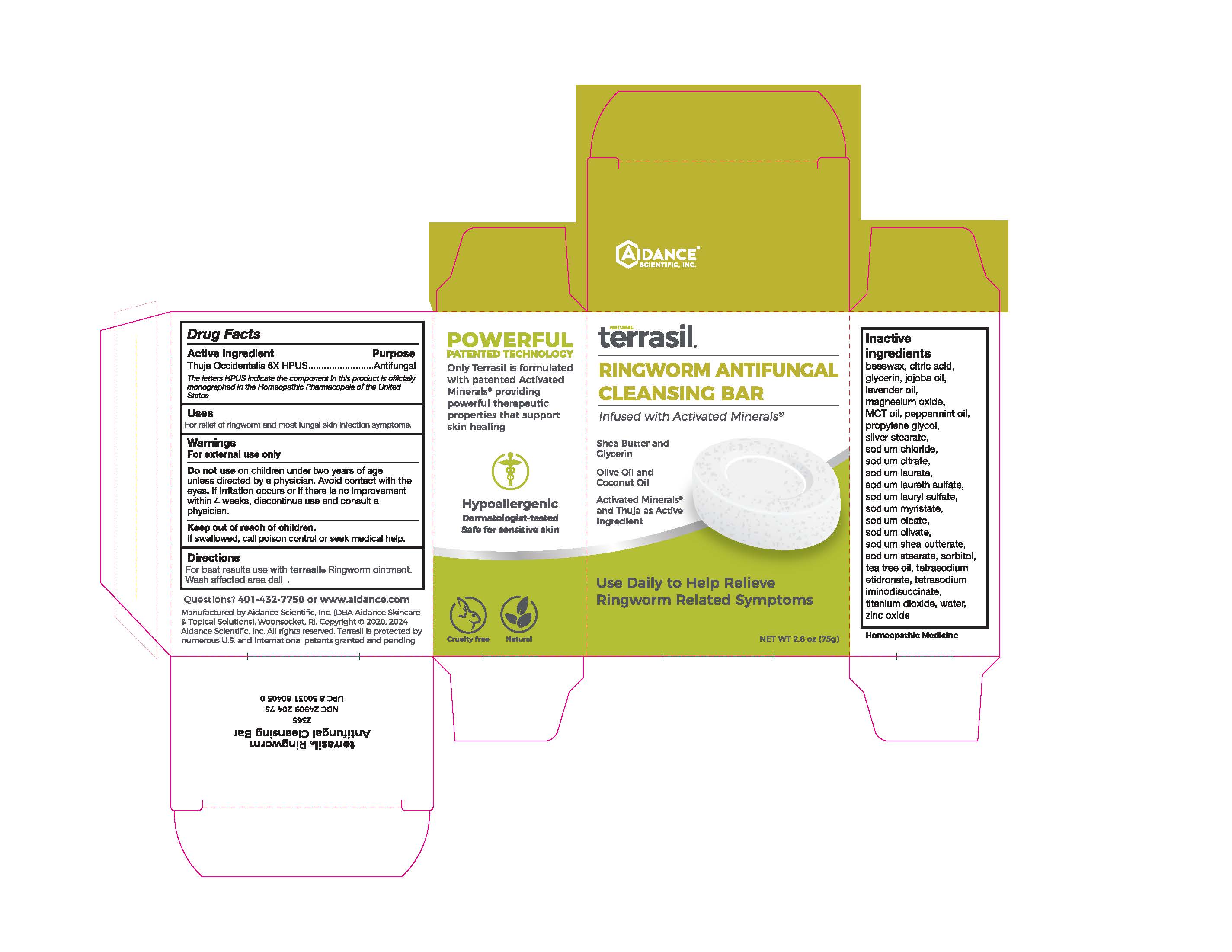 DRUG LABEL: Terrasil Ringworm Anti-Fungal Cleansing Bar 75g
NDC: 24909-204 | Form: SOAP
Manufacturer: Aidance Skincare & Topical Solutions, LLC
Category: homeopathic | Type: HUMAN OTC DRUG LABEL
Date: 20240524

ACTIVE INGREDIENTS: THUJA OCCIDENTALIS WHOLE 6 [hp_X]/1 g
INACTIVE INGREDIENTS: JOJOBA OIL; WATER; SHEA BUTTER; ZINC OXIDE; YELLOW WAX; MEDIUM-CHAIN TRIGLYCERIDES; GLYCERIN; LAVENDER OIL; MAGNESIUM OXIDE; PEPPERMINT OIL; SODIUM CHLORIDE; SODIUM CITRATE; SODIUM LAURATE; SODIUM LAURETH SULFATE; SODIUM LAURYL SULFATE; SODIUM MYRISTATE; SODIUM OLEATE; SODIUM STEARATE; SORBITOL; TEA TREE OIL; TITANIUM DIOXIDE; SILVER STEARATE; SODIUM OLIVATE; ETIDRONATE TETRASODIUM; TETRASODIUM IMINODISUCCINATE; ANHYDROUS CITRIC ACID; PROPYLENE GLYCOL

24909-204 terrasil Ringworm Antifungal Cleansing Bar

Active Ingredient

Thuja Occidentalis 6X HPUS

Purpose

Antifungal

The letters HPUS indicate the component(s) in this product (are) officially monographed in the Homeopathic Pharmacopeia of the United States

Uses

For relief of ringworm and most fungal skin infection symptoms

Warnings

For external use only.
Do not use on children under two years of age unless directed by a physician. Avoid contact with the eyes. If irritation occurs or if there is no improvement within 4 weeks, discontinue use and consult a physician.

Keep out of the reach of children.
If swallowed, call poison control or seek medical help.

Directions

For best results use with terrasil Ringworm ointment. Wash affected area daily.

Inactive Ingredients

beeswax, citric acid, glycerin, jojoba oil, lavender oil, magnesium oxide, MCT oil, peppermint oil, propylene glycol, silver stearate, sodium chloride, sodium citrate, sodium laurate, sodium laureth sulfate, sodium lauryl sulfate, sodium myristate, sodium oleate, sodium olivate, sodium shea butterate, sodium stearate, sorbitol, tea tree oil, tetrasodium etidronate, tetrasodium iminodisuccinate, titanium dioxide, water, zinc oxide

Questions?

401-432-7750 or www.aidance.com